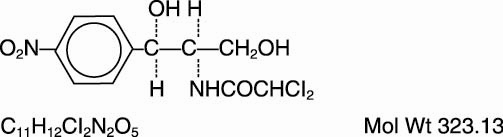 DRUG LABEL: Unknown
Manufacturer: PARKE-DAVIS
Category: prescription | Type: Human prescription drug label
Date: 20061008

Chloromycetin® Ophthalmic Ointment, 1%
(Chloramphenicol Ophthalmic Ointment, USP)

WARNING

Bone marrow hypoplasia including aplastic anemia and death has been reported following topical application of chloramphenicol. Chloramphenicol should not be used when less potentially dangerous agents would be expected to provide effective treatment.

Description

Each gram of Chloromycetin Ophthalmic Ointment, 1% contains 10 mg of chloramphenicol in a special base of liquid petrolatum and polyethylene. It contains no preservatives. Sterile ointment.

The chemical names for chloramphenicol are:

(1) Acetamide, 2,2-dichloro-N-[2-hydroxy-1-(hydroxymethyl)-2-(4-nitrophenyl) ethyl]-, and

(2) D-threo-(—)-2,2-Dichloro-N-[β-hydroxy-α-(hydroxymethyl)-p-nitrophenethyl] acetamide.

Chloramphenicol has the following empirical and structural formulas:

Clinical Pharmacology

Chloramphenicol is a broad-spectrum antibiotic originally isolated from Streptomyces venezuelae. It is primarily bacteriostatic and acts by inhibition of protein synthesis by interfering with the transfer of activated amino acids from soluble RNA to ribosomes. It has been noted that chloramphenicol is found in measurable amounts in the aqueous humor following local application to the eye. Development of resistance to chloramphenicol can be regarded as minimal for staphylococci and many other species of bacteria.

Indications and Usage

Chloramphenicol should be used only in those serious infections for which less potentially dangerous drugs are ineffective or contraindicated. Bacteriological studies should be performed to determine the causative organisms and their sensitivity to chloramphenicol (see Boxed Warning).

Chloromycetin Ophthalmic Ointment, 1% (Chloramphenicol Ophthalmic Ointment, USP) is indicated for the treatment of surface ocular infections involving the conjunctiva and/or cornea caused by chloramphenicol-susceptible organisms.

The particular antiinfective drug in this product is active against the following common bacterial eye pathogens:

Staphylococcus aureus

Streptococcus, including Streptococcus pneumoniae

Escherichia coli

Haemophilus influenzae

Klebsiella/Enterobacter species

Moraxella lucunata

(Morax-Axenfeld bacillus)

Neisseria species

This product does not provide adequate coverage against:

Pseudomonas aeruginosa

Serratia marcescens

Contraindications

This product is contraindicated in persons sensitive to any of its components.

Warnings

SEE BOXED WARNING

Ophthalmic ointments may retard corneal wound healing.

Precautions

GENERAL PRECAUTIONS

The prolonged use of antibiotics may occasionally result in overgrowth of nonsusceptible organisms including fungi. If new infections appear during medication, the drug should be discontinued and appropriate measures should be taken.

In all serious infections the topical use of chloramphenicol should be supplemented by appropriate systemic medication.

Adverse Reactions

Blood dyscrasias have been reported in association with the use of chloramphenicol (see WARNINGS).

Allergic or inflammatory reactions due to individual hypersensitivity and occasional burning or stinging may occur with the use of Chloromycetin Ophthalmic Ointment.

Dosage and Administration

A small amount of ointment placed in the lower conjunctival sac every three hours, or more frequently if deemed advisable by the prescribing physician. Administration should be continued day and night the first 48 hours, after which the interval between applications may be increased. Treatment should be continued for at least 48 hours after the eye appears normal.

How Supplied

N 0071–3070–07

Chloromycetin Ophthalmic Ointment, 1% (Chloramphenicol Ophthalmic Ointment, USP) is supplied, sterile, in ophthalmic ointment tubes of 3.5 grams.

Chloromycetin, brand of chloramphenicol. Reg US Pat Off

Caution—Federal law prohibits dispensing without prescription.

March 1997

©1997, Warner-Lambert Co.

PARKE-DAVIS

Div of Warner-Lambert Co/Morris Plains, NJ 07950 USA